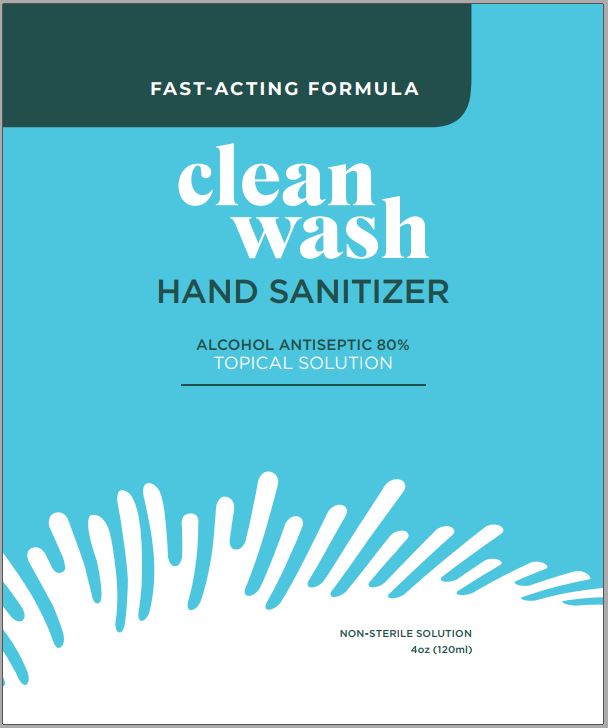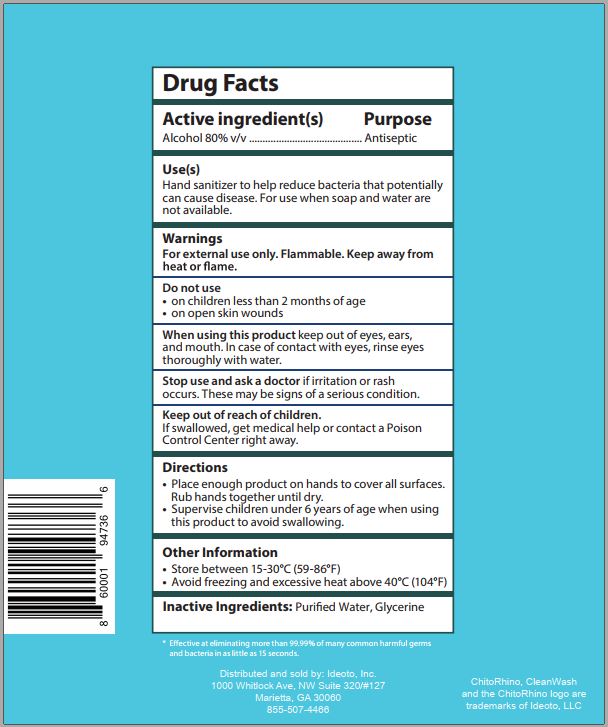 DRUG LABEL: Clean Wash Hand Sanitizer
NDC: 78174-051 | Form: LIQUID
Manufacturer: Custom Chemical Services, LLC
Category: otc | Type: HUMAN OTC DRUG LABEL
Date: 20210413

ACTIVE INGREDIENTS: ALCOHOL 80.0113 L/100 L
INACTIVE INGREDIENTS: GLYCERIN 0.0662 L/100 L; water 19.9226 L/100 L

Active Ingredients

Alcohol 80% v/v

Purpose

Antiseptic

INDICATIONS AND USAGE

Uses Hand sanitizer to help reduce bacteria that potentially can cause disease. For use when soap and water are not available.

WARNINGS

Warning For external use only. Flammable. Keep away from heat or flame.

Do not use

- on children less than 2 months of age
- on open skin wounds

When using this product keep out of eyes, ears, and mouth. In case of contact with eyes, rinse eyes thoroughly with water.

Stop use and ask a doctor if irritation or rash occurs. These may be signs of a serious condition.

Keep out of reach of children.

If swallowed, get medical help or contact a Poison Control Center right away.

Directions

- Place enough product on hands to cover all surfaces. Rub hands together until dry.
- Supervise children under 6 years of age when using this product to avoid swallowing.

Other Information

- Store between 15-30°C (59-86°F)
- Avoid freezing and excessive heat above 40°C (104°F)

Inactive Ingredients Purified water, Glycerin